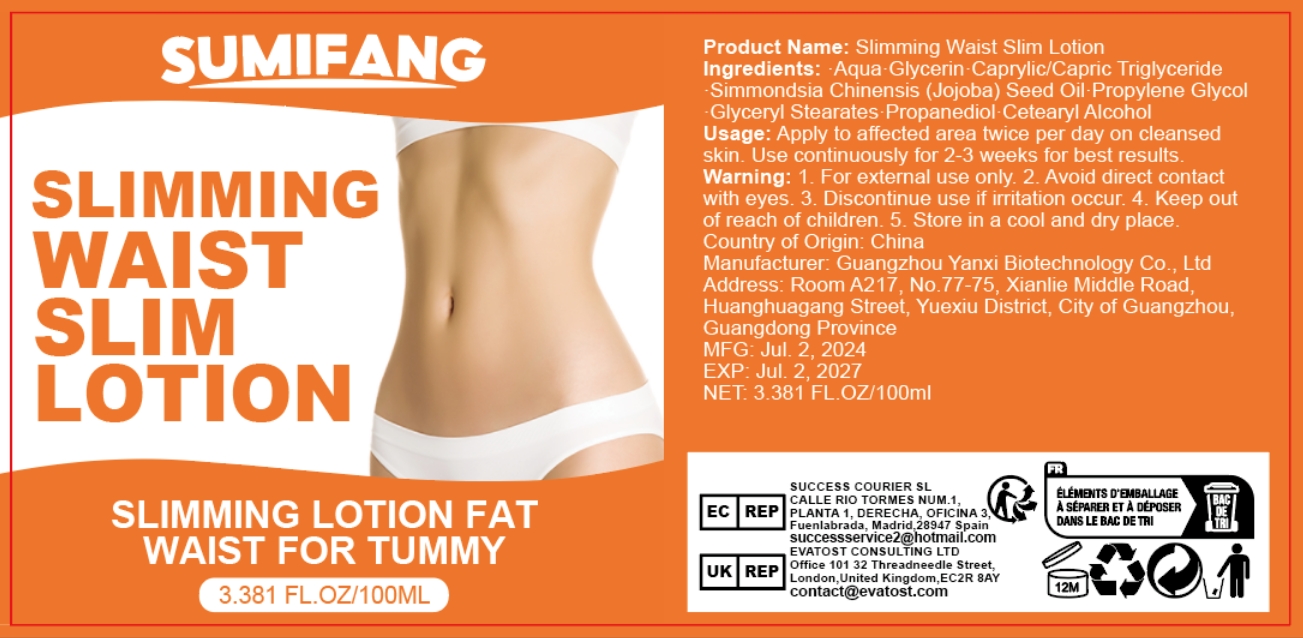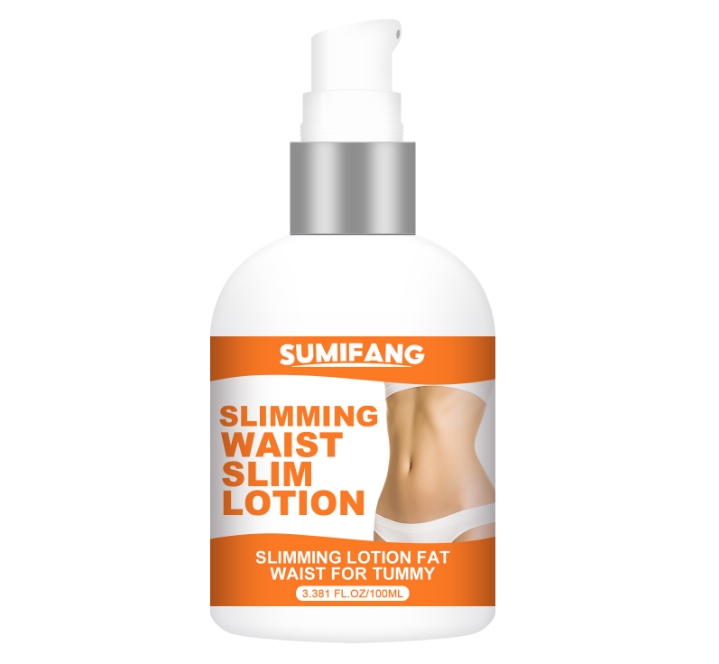 DRUG LABEL: Slimming WaistSlimLotion
NDC: 84025-081 | Form: LOTION
Manufacturer: Guangzhou Yanxi Biotechnology Co., Ltd
Category: otc | Type: HUMAN OTC DRUG LABEL
Date: 20240723

ACTIVE INGREDIENTS: PROPANEDIOL 5 mg/100 mL; GLYCERIN 3 mg/100 mL
INACTIVE INGREDIENTS: WATER

DOSAGE AND ADMINISTRATION

Daub on the waist

INACTIVE INGREDIENT

Aqua

WARNINGS

keep out of children

INDICATIONS AND USAGE

Fat around the waist

keep out of children

PURPOSE

Reduce waist fat, improve the elasticity of waist skin.